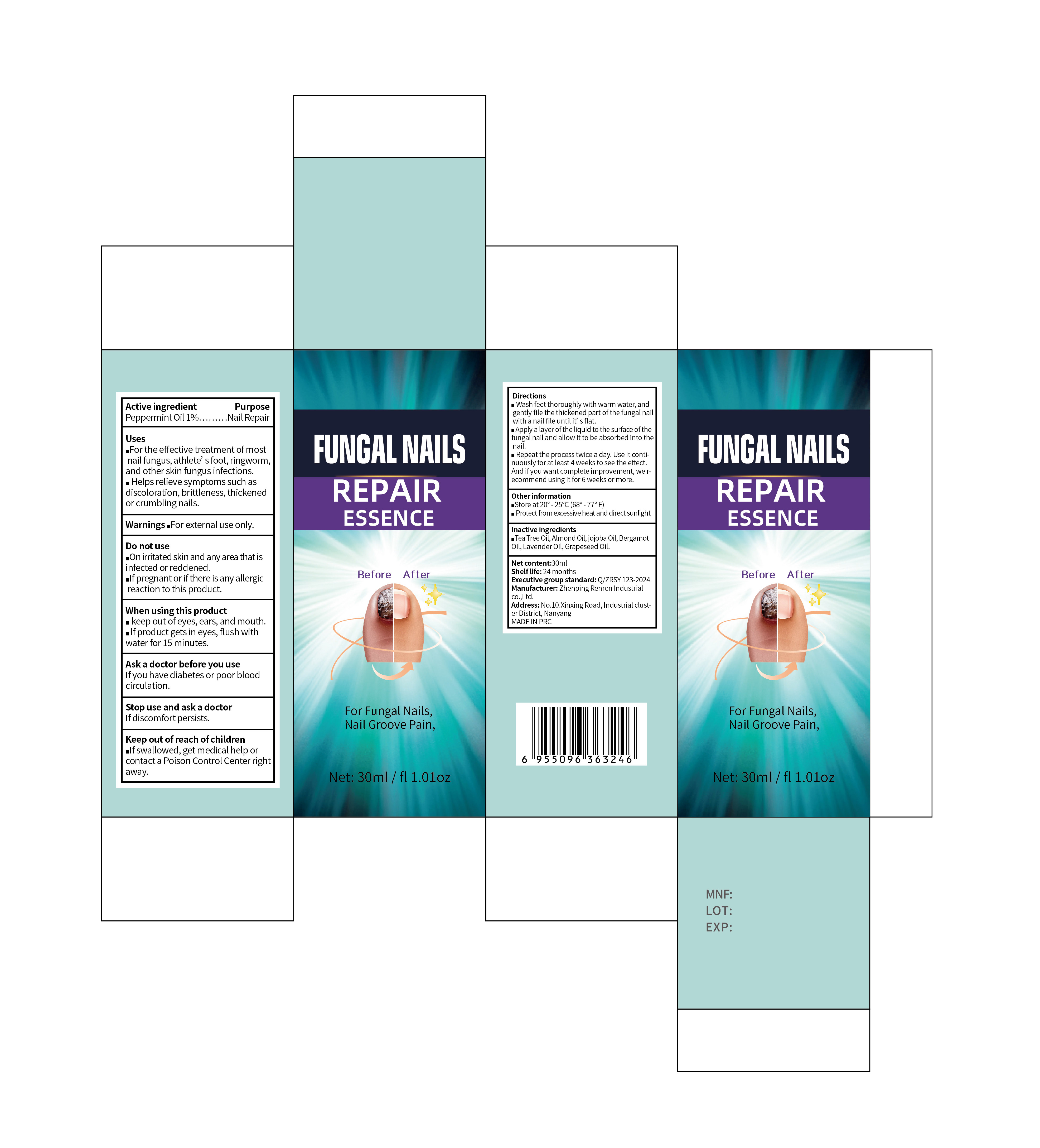 DRUG LABEL: FUNGAL NAILS REPAIRING ESSENCE
NDC: 87096-002 | Form: LIQUID
Manufacturer: Zhenping Renren Industry Co., Ltd.
Category: otc | Type: HUMAN OTC DRUG LABEL
Date: 20250911

ACTIVE INGREDIENTS: PEPPERMINT 1 g/100 g
INACTIVE INGREDIENTS: ALMOND OIL 0.2 g/100 g; JOJOBA OIL 0.1 g/100 g; BERGAMOT OIL 0.1 g/100 g; LAVENDER OIL 0.5 g/100 g; GRAPE SEED OIL 10 g/100 g; TEA TREE OIL 0.1 g/100 g

Active ingredients

Peppermint Oil 1%…………Nail Repair

Purpose

Uses
■For the effective treatment of mostnail fungus,athlete's foot,ringworm,and other skin fungus infections.
■Helps relieve symptoms such as discoloration,brittleness,thickened or crumbling nails.

Uses

■For the effective treatment of mostnail fungus,athlete's foot,ringworm,and other skin fungus infections.
■Helps relieve symptoms such as discoloration,brittleness,thickened or crumbling nails.

Warnings

Warnings: ■For external use only.
Do not use
■On irritated skin and any area that is infected or reddened.
■If pregnant or if there is any allergic reaction to this product.

Stop use and ask a doctor If discomfort persists.

When using this product

■keep out of eyes,ears,and mouth.
■If product gets in eyes,flush with water for 15 minutes.

Ask a doctor before you use If you have diabetes or poor blood circulation.

Keep out of reach of children.If swallowed,get medical help or contact a Poison Control Center right away.

Directions

■Wash feet thoroughly with warm water,and gently file the thickened part of the fungal nail with a nail until it's flat.
■Apply a layer of the liquid to the surface of the fungal nail and allow it to be absorbed into the nail.
■Repeat the process twice a day.Use it continuously for at least 4weeks to see the effect. And if you want complete improvement,we recommend using it for 6 weeks or more.

Other information

■Store at 20°-25℃ (68°-77° F)
■Protect from excessive heat and direct sunlight

Inactive ingredients

Tea Tree Essential Oil,Almond Oil,Jojoba Oil,Bergamot Oil,Lavender Essential Oil,Grape Seed Oil,

DOSAGE & ADMINISTRATION

■Wash feet thoroughly with warm water,and gently file the thickened part of the fungal nail with a nail until it's flat.
■Apply a layer of the liquid to the surface of the fungal nail and allow it to be absorbed into the nail.
■Repeat the process twice a day.Use it continuously for at least 4weeks to see the effect. And if you want complete improvement,we recommend using it for 6 weeks or more.